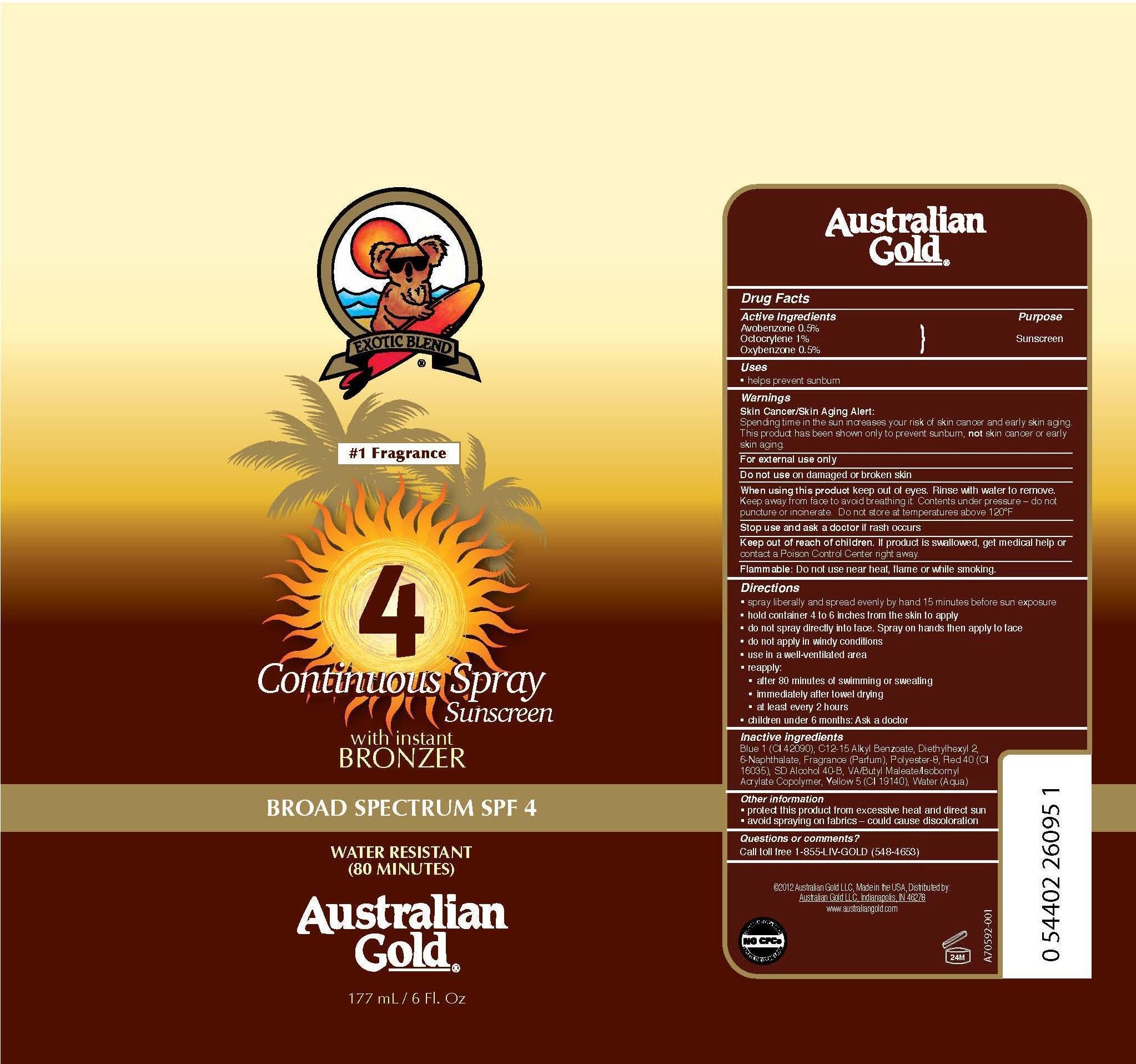 DRUG LABEL: Australian Gold
NDC: 13630-0008 | Form: SPRAY
Manufacturer: Prime Packaging, Inc.
Category: otc | Type: HUMAN OTC DRUG LABEL
Date: 20200117

ACTIVE INGREDIENTS: AVOBENZONE 4.03 mg/1 mL; OCTOCRYLENE 8.06 mg/1 mL; OXYBENZONE 4.03 mg/1 mL
INACTIVE INGREDIENTS: ALKYL (C12-15) BENZOATE; FD&C BLUE NO. 1; DIETHYLHEXYL 2,6-NAPHTHALATE; POLYESTER-8 (1400 MW, CYANODIPHENYLPROPENOYL CAPPED); FD&C RED NO. 40; ALCOHOL; FD&C YELLOW NO. 5; WATER

Active ingredients

Avobenzone 0.5%, Octocrylene 1%, Oxybenzone 0.5%

PURPOSE

Sunscreen

Uses

- helps prevent sunburn

Warnings

Skin Cancer /Skin Aging Alert:

Spending time in the sun increases your risk of skin cancer and early skin aging. This product has been shown only to prevent sunburn, not skin cancer or early skin aging.

OTHER SAFETY INFORMATION

For external use only

Do not use on damaged or broken skin

When using this product keep out of eyes. Rinse with water to remove.Keep away from face to avoid breathing it. Contents under pressure - do not puncture or incinirate. Do not store at temperatures above 120^0F

Stop use and ask a doctor if rash occurs.

Keep out of reach of children. If product is swallowed, get medical help or contact a Poison Control Center right away.

OTHER SAFETY INFORMATION

Flammable: Do not use near heat, flame or while smoking

Directions

- spray liberally and spread evenly by hand 15 minutes before sun exposure
- hold container 4 to 6 inches from the skin to apply
- do not spray directly on face. Spray into hands and apply to face
- do not apply in windy conditions
- use in well-ventilated areas
- reapply:
  - after 80 minutes of swimming or sweating
  - immediately after towel drying
  - at least every 2 hours
- children under 6 months: Ask a doctor

Inactive Ingredients

Blue 1 (CI 42090), C12-15 Alkyl Benzoate, Diethylhexyl 2,6-Naphthalate, Fragrance (Parfum), Polyester-8, Red 40 (CI 16035), SD Alcohol 40-B, VA/Butyl Maleate/Isobornyl Acrylate Copolymer, Yellow 5 (CI 19140), Water (Aqua)

Other information

- protect this product from excesive heat and direct sun
- avoid spraying on fabrics - could cause discoloration

Questions or Comments?

Call toll free 1-855-LIV-GOLD (548-4653)

PRINCIPAL DISPLAY PANEL - 177 mL Can Label

Exotic Blend

#1 Fragrance

4

Continuous Spray Sunscreen

with instant BRONZER

BROAD SPECTRUM SPF 4

WATER RESISTANT(80 MINUTES)

Australian Gold

177 mL / 6 Fl. Oz